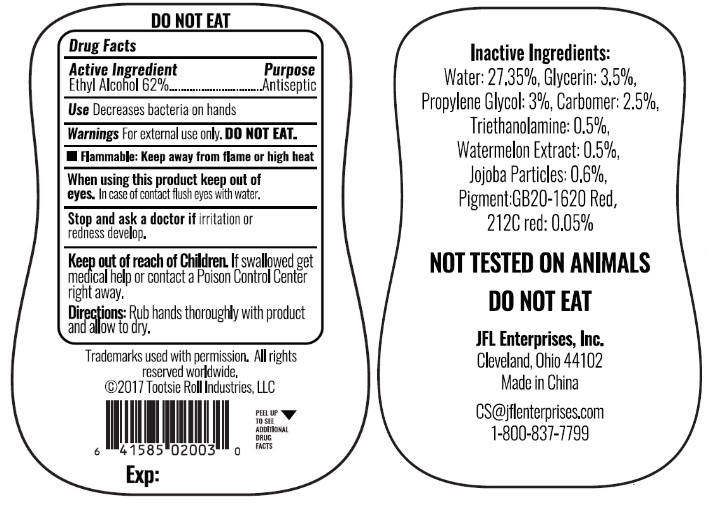 DRUG LABEL: Hand Sanitizer Watermelon
NDC: 71246-4010 | Form: GEL
Manufacturer: JFL ENTERPRISES, INC
Category: otc | Type: HUMAN OTC DRUG LABEL
Date: 20180101

ACTIVE INGREDIENTS: ALCOHOL 62 mL/100 mL
INACTIVE INGREDIENTS: PROPYLENE GLYCOL; WATER; GLYCERIN; CARBOMER HOMOPOLYMER TYPE B (ALLYL SUCROSE CROSSLINKED); TRIETHANOLAMINE 2-CYCLOHEXYL-4,6-DINITROPHENOLATE; PIGMENT RED 1; JOJOBA ACID; WATERMELON

ANTIBACTERIAL HAND GEL Blow Pop Watermelon

Active ingredient

Alcohol 62%

Purpose

Antiseptic Hand Sanitizer

Use

Decrease bacteria on hands

Warnings

External Use Only. DO NOT EAT.

Keep out of reach of children

if swallowed get medical help or contact a Poison Control Center right away.

WARNINGS

Flammable: Keep away from flame or high heat

Directions

Rub hands thoroughly with product and allow to dry.

Inactive Ingredient

Carbomer, Glycerin, Jojoba Particles, Pigment Red GB20-1620, Red 212C, Propylene Glycol, Triethanolamine, Water, Watermelon Extract.

Stop and Ask a doctor if

Irritation or redness develop.